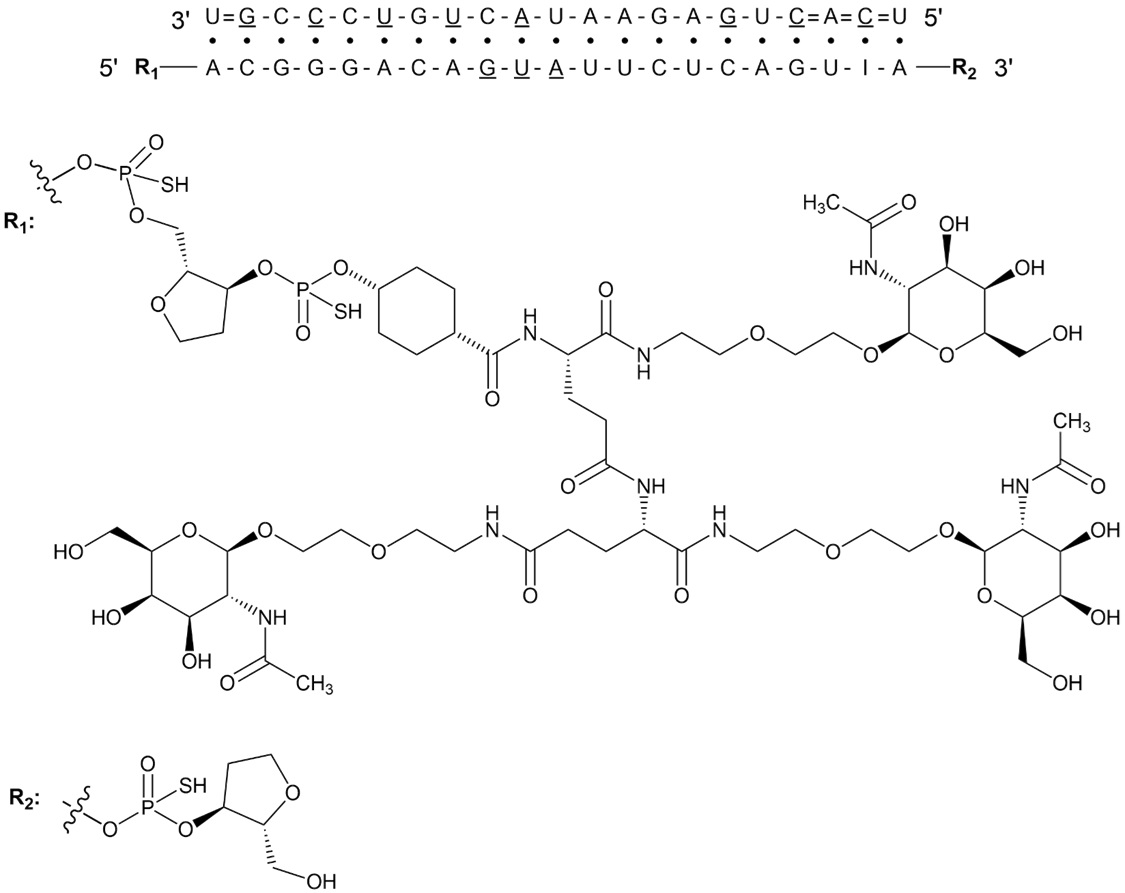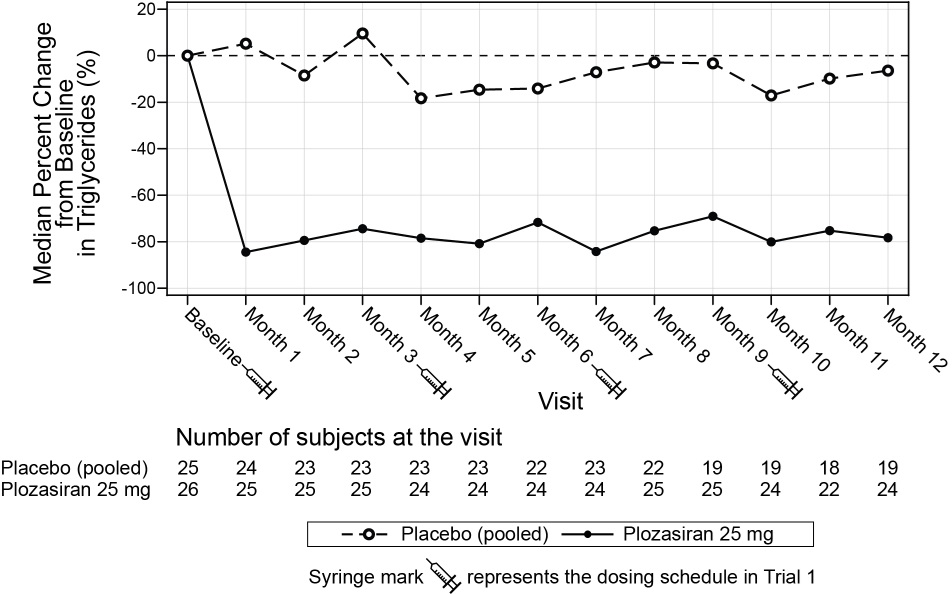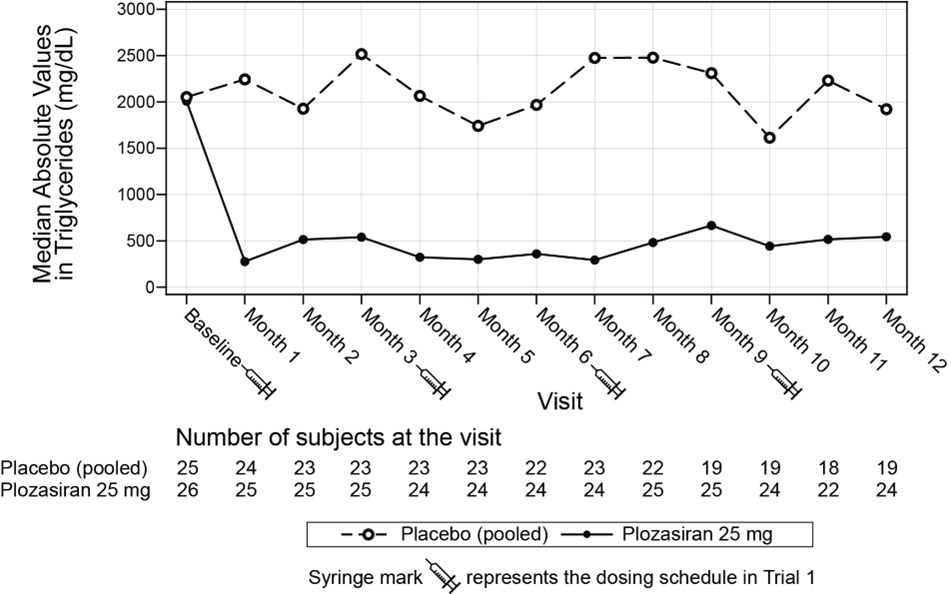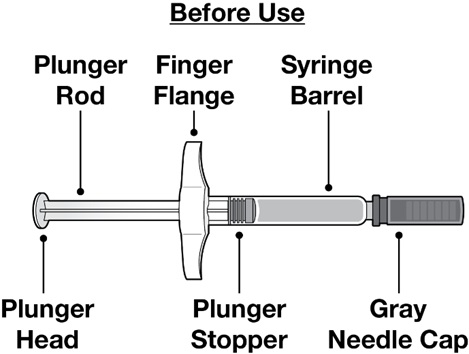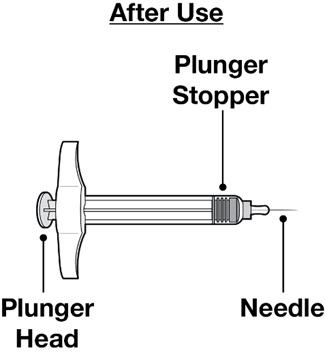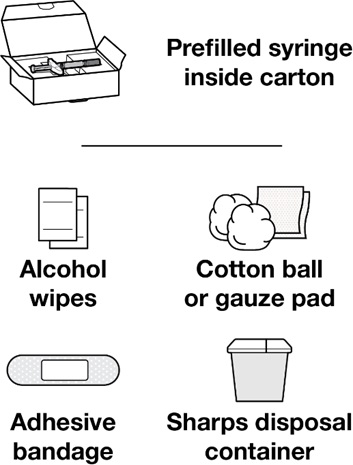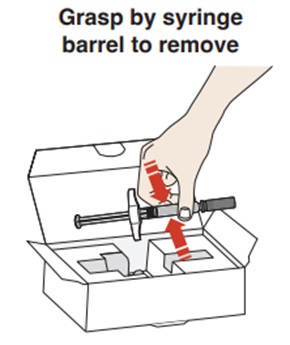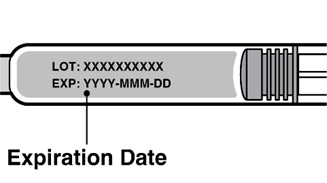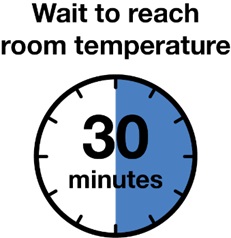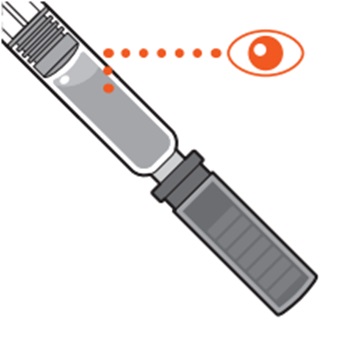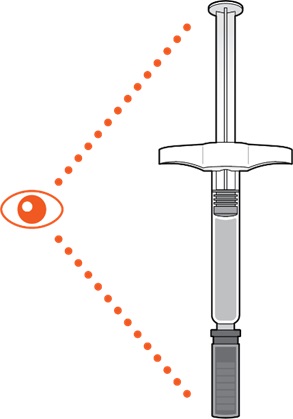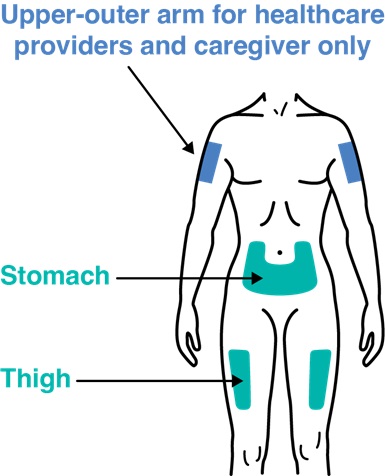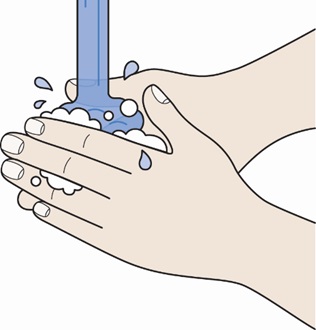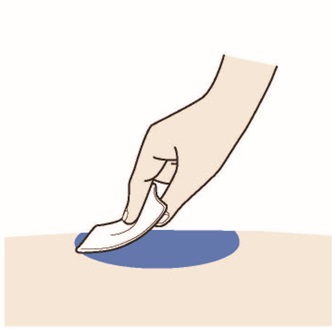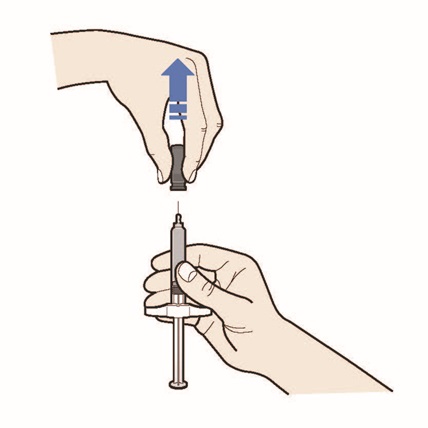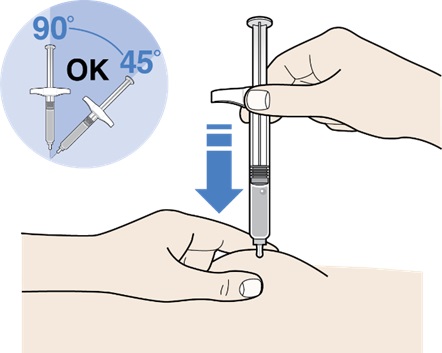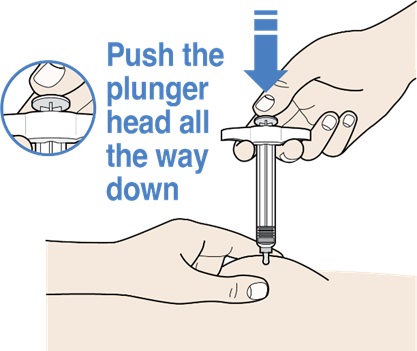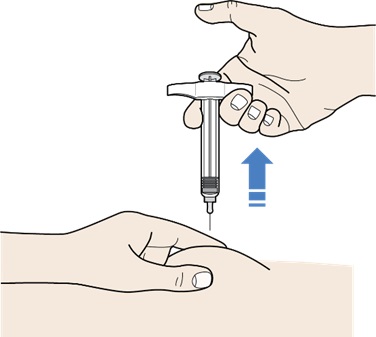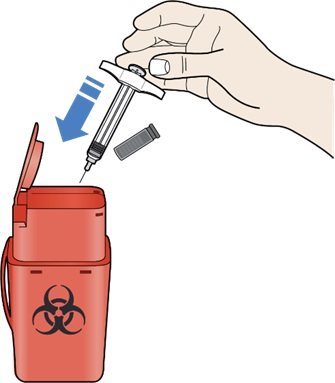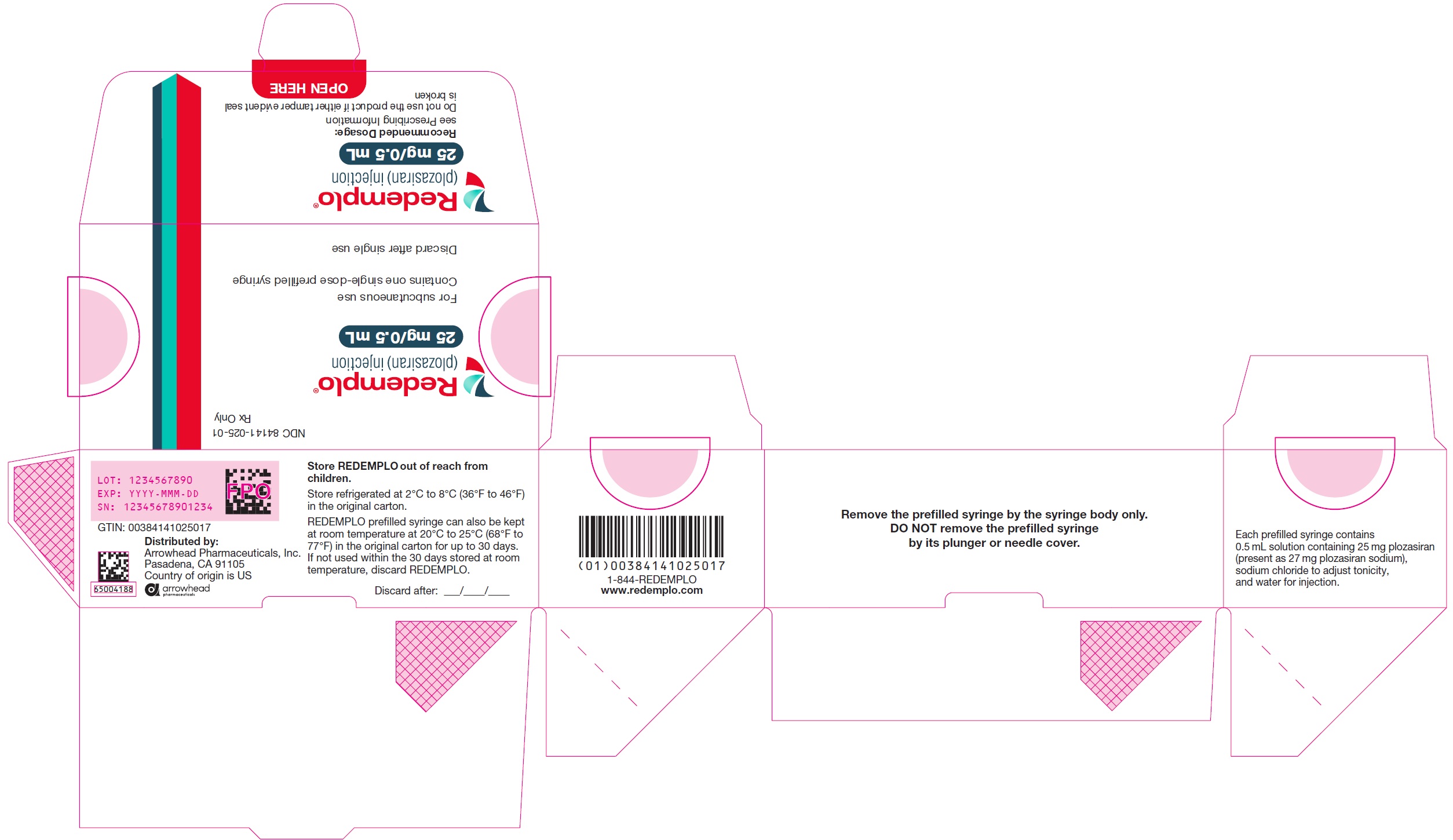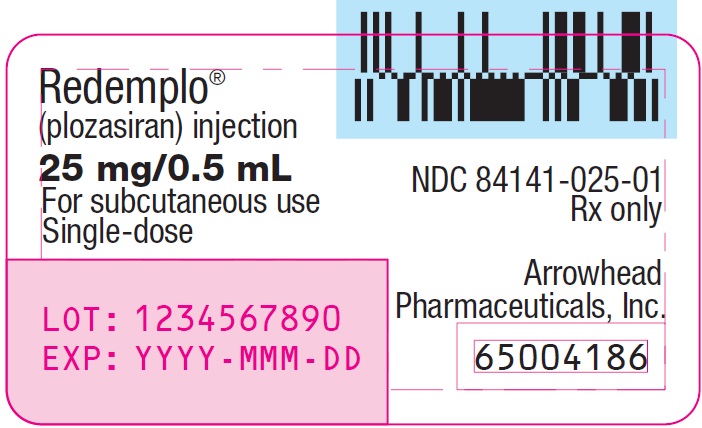 DRUG LABEL: REDEMPLO
NDC: 84141-025 | Form: INJECTION, SOLUTION
Manufacturer: Arrowhead Pharmaceuticals, Inc.
Category: prescription | Type: HUMAN PRESCRIPTION DRUG LABEL
Date: 20251124

ACTIVE INGREDIENTS: PLOZASIRAN 25 mg/0.5 mL

HIGHLIGHTS OF PRESCRIBING INFORMATION

These highlights do not include all the information needed to use REDEMPLO® safely and effectively. See full prescribing information for REDEMPLO.
REDEMPLO (plozasiran) injection, for subcutaneous use
Initial U.S. Approval: 2025

1 INDICATIONS AND USAGE

REDEMPLO is an apolipoprotein C-III (apoC-III)-directed small interfering ribonucleic acid (siRNA) indicated as an adjunct to diet to reduce triglycerides in adults with familial chylomicronemia syndrome (FCS). (1)

2 DOSAGE AND ADMINISTRATION

- The recommended dosage of REDEMPLO is 25 mg injected subcutaneously once every 3 months. (2.1)
- Inject REDEMPLO subcutaneously into the front of the thigh or abdomen. The outer area of the upper arm can be used as an injection site if a healthcare provider or caregiver administers the injection. (2.2)

3 DOSAGE FORMS AND STRENGTHS

Injection: 25 mg/0.5 mL solution in a single-dose pre-filled syringe. (3)

4 CONTRAINDICATIONS

None. (4)

6 ADVERSE REACTIONS

Most common adverse reactions in REDEMPLO treated patients (incidence ≥10% of patients treated with REDEMPLO and >5% more frequently than with placebo) are hyperglycemia, headache, nausea, and injection site reaction. (6.1)

To report SUSPECTED ADVERSE REACTIONS, contact Arrowhead Pharmaceuticals Inc. at 1-844-REDEMPLO (1-844-733-3675), or https://arrowheadpharma.com/safetyreporting, or FDA at 1-800-FDA-1088 or www.fda.gov/medwatch.

FULL PRESCRIBING INFORMATION

1 INDICATIONS AND USAGE

REDEMPLO is indicated as an adjunct to diet to reduce triglycerides in adults with familial chylomicronemia syndrome (FCS).

2 DOSAGE AND ADMINISTRATION

2.1 Recommended Dosage

- The recommended dosage of REDEMPLO is 25 mg injected subcutaneously once every 3 months.

2.2 Important Administration Instructions

- Prior to initiation, train patients and/or caregivers on proper preparation and administration of REDEMPLO [see Instructions for Use].
- Adhere to a low-fat diet (less than or equal to 20 grams fat per day) in conjunction with REDEMPLO.
- Visually inspect the REDEMPLO pre-filled syringe prior to administration. The solution should be clear and colorless to yellow. Do not use if cloudiness, particulate matter, or discoloration is observed prior to administration.
- Inject REDEMPLO subcutaneously into the front of the thigh or abdomen. The outer area of the upper arm can be used as an injection site if a healthcare provider or caregiver administers the injection.
- Do not inject REDEMPLO in an area where the skin is damaged (tender, bruised, red, hard, or cut). Do not inject into areas with scars or stretch marks.
- If a dose is missed, administer REDEMPLO as soon as possible. Resume dosing every 3 months from the date of the most recently administered dose.

3 DOSAGE FORMS AND STRENGTHS

Injection: 25 mg/0.5 mL of plozasiran as a clear and colorless to yellow solution in a single-dose pre-filled syringe.

4 CONTRAINDICATIONS

None.

6 ADVERSE REACTIONS

6.1 Clinical Trials Experience

Because clinical trials are conducted under widely varying conditions, adverse reaction rates observed in the clinical trials of REDEMPLO cannot be directly compared to rates in the clinical trials of another drug and may not reflect the rates observed in practice.

The safety of REDEMPLO was evaluated in 75 patients with FCS enrolled in Trial 1 (NCT05089084) [see Clinical Studies (14)]. In this trial, patients received at least one dose of REDEMPLO 25 mg (N=26) or 50 mg of plozasiran (N=24) and 25 patients received placebo. Plozasiran 50 mg is not an approved dosage regimen for FCS [see Dosage and Administration (2.1)]. Across treatment groups, the mean age was 46 years and 49% of patients were male. Seventy-three percent (73%) of patients were White, 21% were Asian, and 5% were reported as other races; 3% identified as Hispanic or Latino ethnicity. Fifty (50) patients were exposed to REDEMPLO for a median of 11.6 months; 26 patients were treated with REDEMPLO 25 mg every 3 months for a median of 11.8 months.

Adverse reactions led to discontinuation of treatment in 3 (6.0%) of REDEMPLO-treated patients and 0% of placebo-treated patients. The reasons for REDEMPLO treatment discontinuation were hyperglycemia and urticaria. Adverse reactions occurring in greater than or equal to 10% of REDEMPLO-treated patients and greater than 5% more frequently than in placebo-treated patients are listed below in Table 1.

Table 1. Adverse Reactions Occurring in Greater than or Equal to 10% of REDEMPLO-treated Patients and Greater than 5% More Frequently than with Placebo in Trial 1
Adverse Reactions | Placebo (N=25) (%) | REDEMPLO (N=50) (%)
Hyperglycemia^1 | 2 (8%) | 10 (20%)
Headache | 2 (8%) | 8 (16%)
Nausea | 2 (8%) | 7 (14%)
Injection site reaction^1 | 1 (4%) | 5 (10%)
^1Grouped terms composed of several similar terms

Laboratory Tests

Increase in Glucose: Mean increases from baseline in HbA1c (up to 0.36%) and fasting glucose (up to 9 mg/dL) were observed over time in the 25 mg REDEMPLO group. The incidence of hyperglycemia (defined as adverse events consistent with diabetes mellitus or hyperglycemia, new antidiabetic medication, or laboratory values) was higher in 25 mg REDEMPLO-treated patients without a medical history of diabetes at baseline (40%) compared to placebo-treated patients (20%).

Increase in Liver Enzymes: Increases from baseline liver enzymes within the normal range were observed with plozasiran treatment in the FCS population. These increases occurred within the first 3 months of treatment and stabilized.

Increase in LDL-cholesterol: Increases in low-density lipoprotein cholesterol (LDL-C) and total apolipoprotein B (apoB) were observed in the FCS population treated with REDEMPLO compared to those treated with placebo [see Clinical Studies (14)]. Despite increases in the LDL-C, the average LDL-C value at Month 12 was less than 50 mg/dL in the 25 mg REDEMPLO group.

8 USE IN SPECIFIC POPULATIONS

8.1 Pregnancy

Risk Summary

There are insufficient data on REDEMPLO use in pregnant women to inform a drug-associated risk of major birth defects, miscarriage, or adverse maternal or fetal outcomes. Patients with FCS are at risk for pancreatitis during pregnancy because of defects in lipid metabolism and increased triglyceride levels (see Clinical Considerations).

In animal reproduction studies, no adverse drug-related developmental effects were observed in pregnant rats or rabbits with subcutaneous administration of plozasiran during organogenesis up to 23 and 140 times, respectively, the maximum recommended human dose (MRHD) (see Data).

The background risk of major birth defects and miscarriage for the indicated population is unknown. In the U.S. general population, the estimated background risk of major birth defects and miscarriage in clinically recognized pregnancies is 2 to 4% and 15 to 20% respectively.

Clinical Considerations

Disease-Associated Maternal and/or Embryo-Fetal Risk

Triglyceride levels increase during the third trimester of pregnancy. In patients with underlying defects in lipid metabolism, such as FCS, severe gestational hypertriglyceridemia may occur, increasing the risk of acute pancreatitis during pregnancy.

Data

Animal Data

In an embryo-fetal development study, pregnant rats were administered plozasiran by subcutaneous injection at 0, 5, 15, or 60 mg/kg, or 60 mg/kg rat specific surrogate, once daily during the period of organogenesis (gestational days 6 to 17). There was no evidence of drug-related embryo-fetal toxicity or fetal malformations up to 60 mg/kg plozasiran [23 times the MRHD based on body surface area (BSA)]. At maternally toxic doses there were embryo-fetal toxicities including increases in post-implantation loss and mean number of late resorptions at 60 mg/kg (23 times the MRHD based on BSA), early deliveries, reduced fetal body weight, and fetal skeletal developmental variations at ≥15 mg/kg (6 times the MRHD based on BSA). No adverse embryo-fetal developmental effects were observed from a single subcutaneous administration of 50 mg/kg plozasiran (19 times the MRHD based on BSA) or the rat specific surrogate to pregnant rats on gestation day 10.

In an embryo-fetal development study in pregnant rabbits, plozasiran was administered by subcutaneous injection at 0, 30, 60, or 180 mg/kg/day once daily during the period of organogenesis (gestational days 7 to 19). No evidence (of embryo-fetal toxicity or developmental abnormalities) was observed up to 180 mg/kg (140 times the MRHD based on BSA).

In a rat pre- and post-natal development study, plozasiran was administered at 0, 8, 24, or 80 mg/kg by subcutaneous injection once a week from gestation day 6 through lactation day 17. Plozasiran increased the number of females with stillborn offspring and the increase in stillborn offspring per litter resulted in reductions in live birth index at 80 mg/kg (31 times the MRHD based on BSA). There were decreases in offspring body weight and offspring survival at ≥24 mg/kg (9 times the MRHD based on BSA). No adverse effects were noted on offspring development up to 80 mg/kg (31 times the MRHD based on BSA).

8.2 Lactation

Risk Summary

There is no information regarding the presence of plozasiran in human or animal milk, the effects on the breastfed infant, or the effects on milk production. Oligonucleotide-based products typically have poor oral bioavailability. Therefore, it is considered that if plozasiran is present in breastmilk, it is unlikely to lead to clinically relevant levels in breastfed infants. The developmental and health benefits of breastfeeding should be considered along with the mother’s clinical need for REDEMPLO and any potential adverse effects on the breastfed infant from REDEMPLO or from the underlying maternal condition.

8.4 Pediatric Use

The safety and effectiveness of REDEMPLO in pediatric patients with FCS have not been established.

8.5 Geriatric Use

Of the 75 patients with FCS randomized in Trial 1, 9 (12%) were 65 years of age or older, including 2 (3%) patients who were 75 years of age or older. No overall differences in safety or effectiveness of REDEMPLO have been observed between patients 65 years of age and older and younger adult patients.

8.6 Renal Impairment

The recommended dosage of REDEMPLO in patients with mild or moderate renal impairment (eGFR ≥30 to <90 mL/min) is the same as those with normal renal function. The impact of severe renal impairment or end stage renal disease is not known [see Clinical Pharmacology (12.3)].

8.7 Hepatic Impairment

The recommended dosage of REDEMPLO in patients with mild hepatic impairment [total bilirubin ≤1 times the upper limit of normal (ULN) and AST >1 times ULN, or total bilirubin >1.0 to 1.5 times ULN and any AST] is the same as those with normal hepatic function. The impact of moderate or severe hepatic impairment is not known [see Clinical Pharmacology (12.3)].

11 DESCRIPTION

REDEMPLO contains plozasiran (present as plozasiran sodium), a small interfering RNA (siRNA) that degrades apolipoprotein C-III (apoC-III) mRNA by RNA interference. Plozasiran contains a covalently linked ligand containing three N-acetylgalactosamine (GalNAc) residues to facilitate delivery to hepatocytes. The 2´ positions of the ribose subunits in plozasiran are modified with either fluorine (2´F) or methoxy (2´O-Me) groups. Each strand of plozasiran also includes multiple phosphorothioates.

The molecular formula of plozasiran sodium is C493H611F11N164Na43O311P43S7 and its molecular weight is 16,563.98 Da. Plozasiran sodium is freely soluble in water. Plozasiran has the following structural formula:

Abbreviations: A = 2’-O-methyladenosine; A = 2’-fluoro(2’-deoxy-2’-fluoro)adenosine; C = 2’-O-methylcytidine; C = 2’-fluorocytidine; G = 2’-O-methylguanosine; G = 2’-fluoroguanosine; I = 2’-O-methylinosine; U = 2’-O-methyluridine; U = 2’-fluorouridine; - (single line) = phosphodiester linkage; = (double line) = phosphorothioate linkage; · (middle dot) depicts base pairing between the two strands

REDEMPLO is a sterile, preservative-free, clear, colorless to yellow solution for subcutaneous use in a prefilled syringe. Each syringe contains 0.5 mL of solution containing 25 mg plozasiran (present as 27 mg plozasiran sodium), sodium chloride to adjust tonicity, and water for injection.

12 CLINICAL PHARMACOLOGY

12.1 Mechanism of Action

Plozasiran is a siRNA conjugated with GalNAc that degrades the apoC-III mRNA through the RNA interference mechanism resulting in reduced levels of hepatic and serum apoC-III protein. Reduction of apoC-III protein leads to increased clearance of serum triglycerides.

12.2 Pharmacodynamics

In Trial 1 [see Clinical Studies (14)], following the recommended dose of 25 mg administered every 3 months in patients with FCS, REDEMPLO reduced median fasting serum apoC-III protein. The placebo-corrected median percent change in fasting serum apoC-III protein from baseline was -90% at 1 month, -93% at 3 months, -82% at 6 months, -91% at 10 months, and -87% at 12 months.

Cardiac Electrophysiology

At a dose 4 times the recommended dose of 25 mg administered every 3 months, clinically significant QTc interval prolongation was not observed.

12.3 Pharmacokinetics

REDEMPLO exhibited linear and time-invariant pharmacokinetics following subcutaneous injections within the dose range of 10 mg to 100 mg. The following pharmacokinetic parameters were observed in healthy adults after receiving a 25 mg dose of REDEMPLO.

Absorption

Plozasiran peak plasma concentration (Cmax) is 68.5 ng/mL. The median time to reach Cmax (Tmax) is 6 hours.

Distribution

Plozasiran is 78% protein bound in vitro at the clinically relevant plasma concentrations. Following subcutaneous multiple administration of 25 mg plozasiran, the apparent volume of distribution is approximately 146 L. Plozasiran is distributed in plasma and extracellular body water before its uptake by hepatocytes to decrease apoC-III mRNA expression and reduce serum triglycerides.

Elimination

The terminal elimination half-life of plozasiran in plasma is approximately 3 to 4 hours. The mean apparent systemic clearance is 33.8 L/hour.

Metabolism

Plozasiran is primarily metabolized by nucleases to shorter oligonucleotides of varying lengths.

Excretion

Approximately 16 to 19% of REDEMPLO dose is excreted in urine.

Specific Populations

No clinically significant differences in plozasiran pharmacokinetics based on age, sex, race, mild and moderate renal impairment (eGFR ≥30 to <90 mL/min), or mild hepatic impairment (total bilirubin ≤1 times ULN and AST >1 times ULN, or total bilirubin >1.0 to 1.5 times ULN and any AST) were found in the population pharmacokinetic analysis. The impact of severe renal impairment, end-stage renal impairment, or moderate to severe hepatic impairment is not known.

Drug Interaction Studies

In Vitro Assessment of Drug Interactions

CYP450 Enzymes

Plozasiran is not a substrate, inhibitor, or inducer of CYP450 enzymes at clinically relevant concentrations.

Transporter Systems

Plozasiran is not a substrate or an inhibitor of P-gp, BCRP, OAT1, OAT3, OCT1, OCT2, OATP1B1, OATP1B3, MATE1, or MATE2-K.

12.6 Immunogenicity

The observed incidence of anti-drug antibodies (ADAs) is highly dependent on the sensitivity and specificity of the assay. Differences in assay methods preclude meaningful comparisons of the incidence of ADAs in the trial described below with the incidence of anti-drug antibodies in other studies, including those of plozasiran.

In Trial 1, none of the 50 FCS-patients treated with REDEMPLO over a period of 12 months developed treatment-induced or treatment-boosted ADAs. Because ADAs were not observed in the limited number of REDEMPLO-treated patients, the effect of ADAs on the pharmacokinetics, pharmacodynamics, safety, and/or effectiveness of REDEMPLO products is unknown.

13 NONCLINICAL TOXICOLOGY

13.1 Carcinogenesis, Mutagenesis, Impairment of Fertility

Carcinogenesis

In a 26-week study in RasH2Tg mice, plozasiran was administered subcutaneously once every 8 weeks at dose levels of 30, 60, and 120 mg/kg. Plozasiran was not carcinogenic up to the highest tested dose of 120 mg/kg (23-times MRHD based on BSA).

Mutagenesis

Plozasiran was not mutagenic or clastogenic in a standard battery of genetic toxicity assays, including a bacterial mutation (Ames) assay, and in vitro and in vivo mouse micronucleus assays.

Impairment of Fertility

In a fertility and early embryonic-development study, male and female rats were administered subcutaneously with vehicle or plozasiran at the doses of 12.5, 25 or 50 mg/kg or rat specific surrogate at 25 mg/kg. Males were treated once weekly before and throughout cohabitation, while females received treatment either once every 3 days or once weekly before and through mating until gestation day 6. There were no adverse effects on mating and fertility in males or females up to 50 mg/kg corresponding to 19-times the MRHD, based on BSA.

14 CLINICAL STUDIES

The efficacy of REDEMPLO was demonstrated in a randomized, placebo-controlled, double-blind trial in adult patients with genetically confirmed or clinically diagnosed FCS maintained on a low-fat diet(≤20 grams fat per day) (Trial 1; NCT05089084). Patients were randomized to receive four total doses of REDEMPLO 25 mg (n=26) or matching placebo (n=25), injected subcutaneously once every 3 months over a 12-month treatment period

The diagnosis of FCS was based on adults with a screening fasting TG ≥880 mg/dL refractory to lipid-lowering therapy, with a history of elevated triglycerides (in excess of 1,000 mg/dL at least three times), and evidence of FCS by known genotypes, evidence of low lipoprotein lipase activity, or a clinical diagnosis. In this trial, for patients with clinically diagnosed FCS, the inclusion criteria specified at least one of the following: recurrent episodes of acute pancreatitis not caused by alcohol or cholelithiasis; recurrent hospitalizations for severe abdominal pain without other explainable cause; childhood pancreatitis; or family history of hypertriglyceridemia-induced pancreatitis.

Patient demographics were generally similar across the treatment groups [see Adverse Reactions (6.1)]. At enrollment, the percentage of patients with genetic confirmation of FCS was 46% in the REDEMPLO 25 mg group compared with 56% in the placebo group; diabetes was 15% in the REDEMPLO 25 mg group compared with 32% in the placebo group; and a history of documented acute pancreatitis in the prior 5 years was 54% in the REDEMPLO 25 mg group compared with 68% in the placebo group. Patients in the REDEMPLO 25 mg and placebo groups were treated with statins (43%), omega-3 fatty acids (29%), fibrates (69%), or no background TG lowering therapies (25%) at study entry. Mean (SD) and median fasting TG levels at baseline were 2,311 (1,258) mg/dL and 2,030 mg/dL, respectively (range of 747 to 5,596 mg/dL).

The primary efficacy endpoint was percent change in fasting triglycerides from baseline at Month 10 (average of 2 assessments, 2 to 7 days apart). The median difference between REDEMPLO 25 mg and the placebo group in percent change in fasting triglyceride levels from baseline to Month 10 was -58.7% (95% CI: -89.6, -27.9; p< 0.0001). For additional results see Table 2.

Table 2: Baseline and Percent Changes from Baseline in Lipid/Lipoprotein Parameters in Patients with FCS at Month 10 in Trial 1
 | REDEMPLO 25 mg N=26 |  | Placebo (pooled) N=25 |  | REDEMPLO 25 mg vs. Placebo
Parameter (mg/dL) | BL | % change at Month 10 | BL | % change at Month 10 | Treatment Difference % change (95% CI) at Month 10
Triglyceridesbb | 2008 | -80 | 2053 | -17 | -59a (-90, -28)
Non-HDL-Cc | 279 | -39 | 268 | 4 | -42 (-67, -18)
LDL-Cc | 24 | 112 | 28 | 20 | 92 (4, 180)
Total ApoBc | 72 | 27 | 79 | 12 | 15 (-16, 46)
ApoB-48c | 10 | -61 | 11 | 45 | -106 (-180, -33)
Abbreviations: ApoB = apolipoprotein B; CI= confidence interval; BL = baseline; FCS=familial chylomicronemia syndrome; non-HDL-C = non-high-density lipoprotein cholesterol; LDL-C = low-density lipoprotein cholesterol.
a Reached statistical significance (p value ˂ 0.0001).
b Median; Hodges-Lehmann method was used to estimate the median difference (location shift) and its corresponding 95% confidence interval for percent changes. Missing data were imputed using washout imputation.
c Mean; Analysis of covariance (ANCOVA) model was used to estimate the mean difference and its corresponding 95% confidence interval for percent changes. Missing data were imputed using washout imputation.

Median percent change in TG from baseline (Figure 1) and median absolute TG values (Figure 2) over time demonstrated a consistent lowering effect during the 12-month treatment period.

Figure 1: Median Percent Change from Baseline in Fasting Triglycerides Over Time in Trial 1

Figure 2: Median Absolute Fasting Triglyceride Levels (mg/dL) in Trial 1

Over the 12-month treatment period, the numerical incidence of acute pancreatitis in patients treated with REDEMPLO 25 mg was lower compared with placebo [2 (8%) patients in the REDEMPLO 25 mg group compared with 5 (20%) patients in the placebo group].

16 HOW SUPPLIED/STORAGE AND HANDLING

REDEMPLO injection is a clear and colorless to yellow solution supplied in a single-dose prefilled syringe. Each prefilled syringe of REDEMPLO is filled to deliver 0.5 mL of solution containing 25 mg of plozasiran.

REDEMPLO is available in cartons containing one 25 mg single-dose prefilled syringe each (NDC 84141-025-01).

Storage

Store REDEMPLO refrigerated at 2°C to 8°C (36°F to 46°F) in the original carton, until ready for use.

REDEMPLO prefilled syringe can also be kept at room temperature at 20°C to 25°C (68°F to 77°F) in the original carton for up to 30 days. If not used within the 30 days stored at room temperature, discard REDEMPLO.

17 PATIENT COUNSELING INFORMATION

Advise the patient to read the FDA-approved patient labeling (Patient Information and Instructions for Use).

Adherence to Diet

Advise patients with FCS that use of lipid-regulating agents does not reduce the importance of adhering to a low-fat diet (less than or equal to 20 grams fat per day) [see Dosage and Administration (2.2)].

Missed Dose

Instruct patients to take REDEMPLO as prescribed. If a dose is missed, instruct patients to take as soon as they remember. Resume dosing every 3 months from the date of the most recently administered dose [see Dosage and Administration (2.2)].

Distributed by:
Arrowhead Pharmaceuticals, Inc.
Pasadena, CA 91105
© 2025, Arrowhead Pharmaceuticals, Inc.
All rights reserved.
REDEMPLO is a registered trademark of Arrowhead Pharmaceuticals, Inc.

PATIENT INFORMATION
REDEMPLO® [ree-DEM-plo]
(plozasiran)
injection, for subcutaneous use

Read this Patient Information carefully before you start taking REDEMPLO. If you have any questions about REDEMPLO, ask your healthcare provider.

What is REDEMPLO?

- REDEMPLO is an injectable prescription medicine used together with a low-fat diet to reduce triglycerides (fat in the blood) in adults with a condition that keeps the body from breaking down fats called familial chylomicronemia syndrome (FCS).
- It is not known if REDEMPLO is safe and effective in children.

Before using REDEMPLO, tell your healthcare provider about all of your medical conditions, including if you:

- are pregnant or plan to become pregnant. It is not known if REDEMPLO can harm your unborn baby. Tell your healthcare provider if you become pregnant while using REDEMPLO.
- are breastfeeding or plan to breastfeed. It is not known if REDEMPLO passes into your breast milk and if it can harm your baby. Talk with your healthcare provider about the best way to feed your baby while using REDEMPLO.

Tell your healthcare provider about all of the medicines you take including prescription and over-the-counter medicines, vitamins, and herbal supplements. Know the medicines you take. Keep a list of them to show your healthcare provider and pharmacist when you get a new medicine.

How should I use REDEMPLO?

- Read the Instructions for Use that comes with your REDEMPLO pre-filled syringe.
- Your healthcare provider will show you and/or your caregiver(s) how to inject REDEMPLO the first time.
- REDEMPLO is injected under the skin (subcutaneous use) in the front of your upper legs (thighs) or in your stomach area (abdomen). Only your healthcare provider or caregiver(s) may give you an injection in the outer area of your upper arm.
- REDEMPLO should be injected 1 time every 3 months.
- If you miss a dose, take the missing dose as soon as possible. Then inject REDEMPLO 3 months from the date of your last dose to get back on the every-3-month dosing schedule.
- Stay on a low-fat diet (less than or equal to 20 grams of fat each day) while using REDEMPLO.

What are the possible side effects of REDEMPLO?

The most common side effects of REDEMPLO include:

- high blood sugar (hyperglycemia)
- headache
- nausea
- injection site reaction (pain, redness, or swelling)

These are not all of the possible side effects of REDEMPLO. Tell your healthcare provider if you have any of the above side effects. Call your health care provider for medical advice about side effects. You may report side effects to FDA at 1-800-FDA-1088 or by calling 1-844-REDEMPLO (1-844-733-3675) or via https://arrowheadpharma.com/safetyreporting.

How should I store REDEMPLO?

- Store REDEMPLO prefilled syringe in the refrigerator between 36°F to 46°F (2°C to 8°C) in the original carton, until you are ready to use.
- REDEMPLO can also be stored at room temperature between 68°F to 77°F (20°C to 25°C) in the original carton for up to 30 days.
- Throw away the REDEMPLO prefilled syringe if kept at room temperature longer than 30 days.

General information about the safe and effective use of REDEMPLO.

Medicines are sometimes prescribed for purposes other than those listed in a Patient Information Leaflet. Do not use REDEMPLO for a condition for which it was not prescribed. Do not give REDEMPLO to other people, even if they have the same symptoms that you have. It may harm them. You can ask your pharmacist or healthcare provider for information about REDEMPLO that is written for health professions.

What are the ingredients in REDEMPLO?

Active ingredients: plozasiran sodium

Inactive ingredients: sodium chloride, water for injection

Distributed by:
Arrowhead Pharmaceuticals, Inc.
Pasadena, CA 91105
©2025, Arrowhead Pharmaceuticals, Inc.
All rights reserved.

This Patient Information has been approved by the U.S. Food and Drug Administration.

Approved: 11/2025

INSTRUCTIONS FOR USE

REDEMPLO® [ree-DEM-plo]
(plozasiran)
injection, for subcutaneous use
single-dose prefilled syringe
25 mg/0.5 mL

This Instructions for Use contains information on how to inject REDEMPLO (plozasiran).
Read this Instructions for Use before you start using your REDEMPLO prefilled syringe and each time you get a refill. There may be new information. This information does not take the place of talking to your healthcare provider about your medical condition or your treatment. Your healthcare provider should show you or your caregiver how to use your REDEMPLO prefilled syringe the right way. Call your healthcare provider or pharmacist if you have any questions.

Guide to Parts

Each carton contains a single-dose REDEMPLO (plozasiran) Injection prefilled syringe for single use under the skin (subcutaneous) injection.

Important Information You Need to Know Before Injecting REDEMPLO

- REDEMPLO is for subcutaneous injection only
- Each carton contains a 1-time (single-dose) REDEMPLO (plozasiran) prefilled syringe.
- Do not use your REDEMPLO single-dose prefilled syringe if the carton appears damaged or the tamper evident seal on the carton is broken.
- Do not remove the gray needle cap until you are ready to inject (Step 6).
- Do not use if the single-dose prefilled syringe appears damaged.
- Throw away (dispose of) your REDEMPLO prefilled syringe in a sharps disposal container right away after use (Step 10: Disposing of REDEMPLO).

Storing REDEMPLO

- Keep the REDEMPLO prefilled syringe in the original carton until ready to use.
- Store the REDEMPLO prefilled syringe in the refrigerator between 36°F to 46°F (2°C to 8°C) in the original carton.
- REDEMPLO prefilled syringe can also be stored at room temperature between 68°F to 77°F (20°C to 25°C) in the original carton for up to 30 days.
- Do not let REDEMPLO reach temperatures above 77°F (25°C).
- Throw away the REDEMPLO prefilled syringe if kept at room temperature and not used within 30 days.

If the product is not stored in any of the above conditions, throw away the prefilled syringe in a sharps disposal container and use a new prefilled syringe.

Keep REDEMPLO prefilled syringe and all medicine out of reach of children.

Preparing to Inject REDEMPLO

Step 1: Gather all materials needed for your REDEMPLO injection

Figure A

On a clean, well-lit, flat work surface, place:
Provided in the carton (see Figure A):

- 1 REDEMPLO prefilled syringe

Other materials not provided (see Figure A):

- Alcohol wipes
- Cotton ball or gauze pad
- Adhesive bandage
- Sharps disposal container

Step 2: Prepare to use REDEMPLO prefilled syringe

Figure B

Figure C

Figure D

- If refrigerated, remove the carton from the refrigerator.
- Open the carton lid and remove the syringe by the syringe barrel and place on a flat surface (see Figure B).
  - Do not use the prefilled syringe if tamper evident seal on the carton is broken.
  - Do not pick up or pull the prefilled syringe by the plunger rod or gray needle cap.
- Check the expiration date on the REDEMPLO prefilled syringe. (see Figure C).
  - Do not use if the expiration date has passed.
- Wait 30 minutes for the prefilled syringe to reach room temperature before injecting (see Figure D).
  - Do not try to warm the prefilled syringe by using a heat source such as hot water or a microwave.
  - Do not remove the gray needle cap from the prefilled syringe until you are ready to inject.

Step 3: Check the medicine and syringe

Figure E

Figure F

- Check the the REDEMPLO medicine in the prefilled syringe (see Figure E).
  - The medicine should be clear and colorless to yellow.
    - Do not use the prefilled syringe if the medicine is cloudy, discolored or contains particles.
  - It is normal to see air bubbles in the medicine.

- Inspect the prefilled syringe (see Figure F).
  - Do not use the prefilled syringe if any part appears cracked or broken.
  - Do not use the prefilled syringe if the gray needle cap is missing or not securely attached.
  - Do not use the prefilled syringe if it has been dropped onto a hard surface because the syringe may be damaged.
- In any of the above cases, call 1-844-REDEMPLO or visit www.redemplo.com.

Injecting REDEMPLO

Step 4: Choose your injection site

Figure G

- Choose an injection site on the (see Figure G):
  - Upper leg (thigh) or
  - Stomach (abdomen) except for a 2-inch area right around the belly button (navel).

Only your healthcare providers or caregivers can use the outer area of the upper arm (see Figure G).

- Do not inject:
  - within 2 inches of the belly button (navel).
  - into skin that is damaged (tender, bruised, red, hard, or cut).
  - into areas with scars, stretch marks.

Step 5: Wash hands and clean the injection site

Figure H

Figure I

- Wash your hands thoroughly with soap and water (see Figure H).
- Clean your injection site with an alcohol wipe. Let your skin dry before injecting (see Figure I).
  - Do not touch the cleaned skin before injecting.

Step 6: Remove the needle cap

Figure J

- Hold the prefilled syringe by the syringe barrel, with the needle facing away from you.
- Pull the gray needle cap straight up and away from your body (see Figure J).
  - Do not twist or bend the gray needle cap.
  - Avoid pushing the plunger head before you are ready to inject.
    - Do not let the needle touch any surface.
    - Do not put the needle cap back onto your prefilled syringe.

Step 7: Pinch the skin and Insert the needle

Figure K

- Hold your prefilled syringe by the finger flange in one hand.
- Gently pinch and hold a fold of skin at the injection site with your other hand.
- Insert needle at a 45°(degree) to 90° angle (see Figure K).
- Keep the skin pinched while you are inserting the needle and during injection.
  - Do not place your finger on the plunger head before the injection.

Step 8: Hold skin pinch and Push down the plunger head

Figure L

- While pinching the skin, push the plunger head all the way down using slow and constant pressure (see Figure L).

Step 9: Complete the Injection

Figure M

- After the plunger head is pushed all the way down, take the needle out of the skin, by gently lifting the syringe up and off the skin until the needle is completely removed (see Figure M).
  - Do not pull the plunger head up. Lift the whole syringe straight up.
  - Do not rub the injection site.
- There may be a small amount of blood or liquid where you injected. This is normal.
  - If needed, press a cotton ball or gauze pad on the area and apply an adhesive bandage.
- Place the used cap and syringe in a sharps disposal container right away (see section – “Disposing of REDEMPLO”).
  - Do not put the needle cap back onto the syringe.

Step 10: Disposing of REDEMPLO

Figure N

Do not use any medicine that is left in the used syringe.

- Put your used syringes and needle cap in an FDA-cleared sharps disposal container right away after use.
- Do not throw away (dispose of) loose needles and syringes in your household trash (see Figure N).
- If you do not have an FDA-cleared sharps disposal container, you may use a household container that is:
  - made of a heavy-duty plastic,
  - can be closed with a tight-fitting, puncture-resistant lid, without sharps being able to come out,
  - upright and stable during use,
  - leak-resistant, and
  - properly labeled to warn of hazardous waste inside the container.
- When your sharps disposal container is almost full, you will need to follow your community guidelines for the right way to dispose of your sharps disposal container. There may be state or local laws about how you should throw away used needles and syringes.
- For more information about safe sharps disposal, and for specific information about sharps disposal in the state that you live in, go to the FDA's website at: http://www.fda.gov/safesharpsdisposal.

Do not dispose of your used sharps disposal container in your household trash unless your community guidelines permit this. Do not recycle your used sharps disposal container.

For more information, call 1-844-REDEMPLO or visit www.redemplo.com.

Distributed by:
Arrowhead Pharmaceuticals, Inc.
Pasadena, CA 91105
Phone Number: 1-844-REDEMPLO

This Instructions for Use has been approved by the U.S. Food and Drug Administration.

Approved: 11/2025